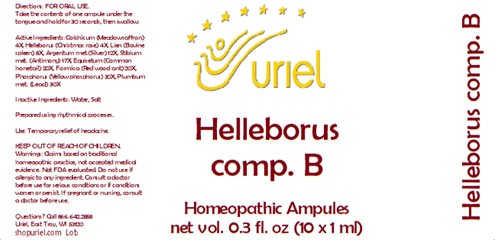 DRUG LABEL: Helleborus comp. B
NDC: 48951-5115 | Form: LIQUID
Manufacturer: Uriel Pharmacy Inc.
Category: homeopathic | Type: HUMAN OTC DRUG LABEL
Date: 20241217

ACTIVE INGREDIENTS: COLCHICUM AUTUMNALE WHOLE 4 [hp_X]/1 mL; FORMICA RUFA 20 [hp_X]/1 mL; BOS TAURUS SPLEEN 8 [hp_X]/1 mL; ANTIMONY 17 [hp_X]/1 mL; SILVER 12 [hp_X]/1 mL; HELLEBORUS FOETIDUS ROOT 4 [hp_X]/1 mL; EQUISETUM ARVENSE TOP 20 [hp_X]/1 mL; PHOSPHORUS 30 [hp_X]/1 mL; LEAD 30 [hp_X]/1 mL
INACTIVE INGREDIENTS: WATER; SODIUM CHLORIDE

Helleborus comp. B

INDICATIONS AND USAGE

Directions: FOR ORAL USE.

DOSAGE AND ADMINISTRATION

Take the contents of one ampule under the tongue and hold for 30 seconds, then swallow.

ACTIVE INGREDIENT

Active Ingredients: Colchicum (Meadow saffron) 4X, Helleborus (Christmas rose) 4X, Lien (Bovine spleen) 8X, Argentum (Silver) 12X, Stibium (Antimony) 17X, Equisetum (Common horsetail) 20X, Formica (Red wood ant) 20X, Phosphorus (Yellow phosphorus) 30X, Plumbum (Lead) 30X

Inactive Ingredients: Water, Salt

Prepared using rhythmical processes.

KEEP OUT OF REACH OF CHILDREN.

WARNINGS

Warnings: Claims based on traditional homeopathic practice, not accepted medical evidence. Not FDA evaluated. Do not use if allergic to any ingredient. Consult a doctor before use for serious conditions or if conditions worsen or persist. If pregnant or nursing, consult a doctor before use.

Questions? Call 866.642.2858
Uriel, East Troy, WI 53120
shopuriel.com Lot: